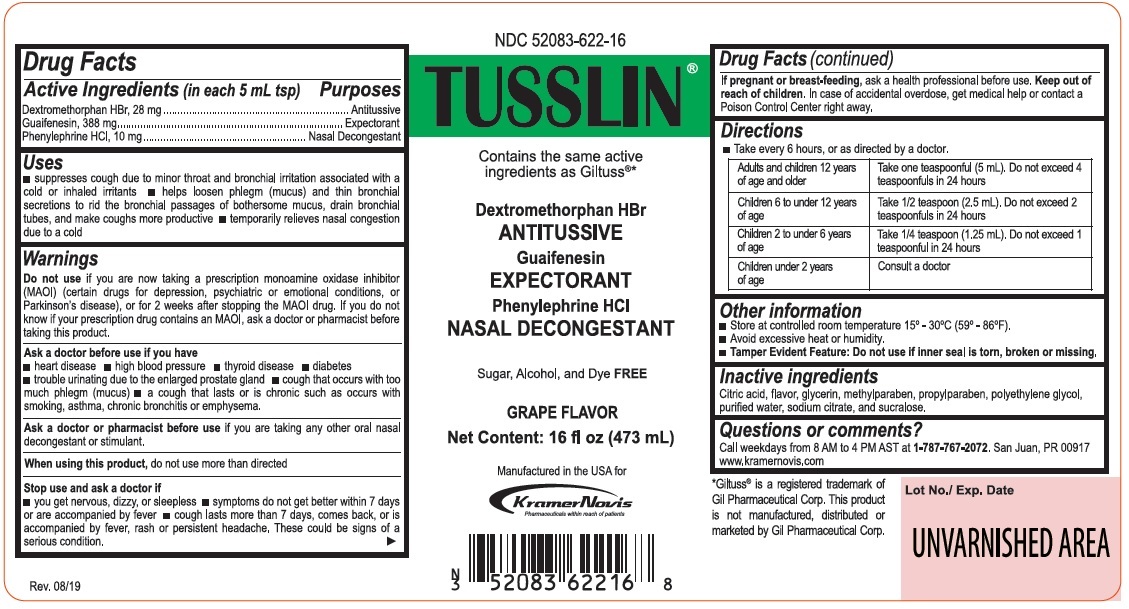 DRUG LABEL: Tusslin
NDC: 52083-622 | Form: SYRUP
Manufacturer: Kramer Novis
Category: otc | Type: HUMAN OTC DRUG LABEL
Date: 20221015

ACTIVE INGREDIENTS: DEXTROMETHORPHAN HYDROBROMIDE 28 mg/5 mL; GUAIFENESIN 388 mg/5 mL; PHENYLEPHRINE HYDROCHLORIDE 10 mg/5 mL
INACTIVE INGREDIENTS: CITRIC ACID MONOHYDRATE; GLYCERIN; METHYLPARABEN; PROPYLPARABEN; POLYETHYLENE GLYCOL 1450; POLYETHYLENE GLYCOL 400; WATER; SODIUM CITRATE, UNSPECIFIED FORM; SUCRALOSE

TUSSLIN®

Active Ingredients (in each 5 mL tsp)

Dextromethorphan HBr, 28 mg

Guaifenesin, 388 mg

Phenylephrine HCl, 10 mg

Purposes

Antitussive

Expectorant

Nasal Decongestant

Uses

- suppresses cough due to minor throat and bronchial irritation associated with a cold or inhaled irritants • helps loosen phlegm (mucus) and thin bronchial secretions to rid the bronchial passages of bothersome mucus, drain bronchial tubes, and make cough more productive • temporarily relieves nasal congestion due to a cold

Warnings

Do not use if you are now taking a prescription monoamine oxidase inhibitor (MAOI) (certain drugs for depression, psychiatric or emotional conditions, or Parkinson’s disease), or for 2 weeks after stopping the MAOI drug. If you do not know if your prescription drug contains an MAOI, ask a doctor or pharmacist before taking this product.

Ask a doctor before use if you have
• heart disease • high blood pressure • thyroid disease • diabetes • trouble urinating due to the enlarged prostate gland • cough that occurs with too much phlegm (mucus) • a cough that lasts or is chronic such as occurs with smoking, asthma, chronic bronchitis or emphysema.

Ask a doctor or pharmacist before use if you are taking any other oral nasal decongestant or stimulant.

When using this product, do not use more than directed

Stop use and ask a doctor if
• you get nervous, dizzy, or sleepless • symptoms do not get better within 7 days or are accompanied by fever • cough lasts more than 7 days, comes back, or is accompanied by fever, rash or persistent headache. These could be signs of a serious condition.

If pregnant or breast-feeding, ask a health professional before use.

Keep out of reach of children. In case of accidental overdose, get medical help or contact a Poison Control Center right away.

Directions

• Take every 6 hours, or as directed by a doctor.

Adults and children 12 years of age and older | Take one teaspoonful (5 mL). Do not exceed 4 teaspoonfuls in 24 hours
Children 6 to under 12 years of age | Take 1/2 teaspoonful (2.5 mL). Do not exceed 2 teaspoonfuls in 24 hours
Children 2 to under 6 years of age | Take 1/4 teaspoonful (1.25 mL). Do not exceed 1 teaspoonful in 24 hours
Children under 2 years of age | Consult a doctor

Other information

- Store at controlled room temperature 15°-30°C (59°-86°F).
- Avoid excessive heat or humidity.
- Tamper Evident Feature: Do not use if inner seal is torn, broken or missing.

Inactive ingredients

Citric acid, flavor, glycerin, methylparaben, propylparaben, polyethylene glycol, purified water, sodium citrate, and sucralose.

Questions or comments?

Call weekdays from 8 AM to 4 PM AST at 1-787-767-2072. San Juan, PR 00917
www.kramernovis.com

NDC 52083-622-16

Contains the same active ingredients as Giltuss®*

Sugar, Alcohol, and Dye FREE

GRAPE FLAVOR

Manufactured in the USA for

Kramer Novis

*Giltuss® is a registered trademark of Gil Pharmaceutical Corp. This product is not manufactured, distributed or marketed by Gil Pharmaceutical Corp.